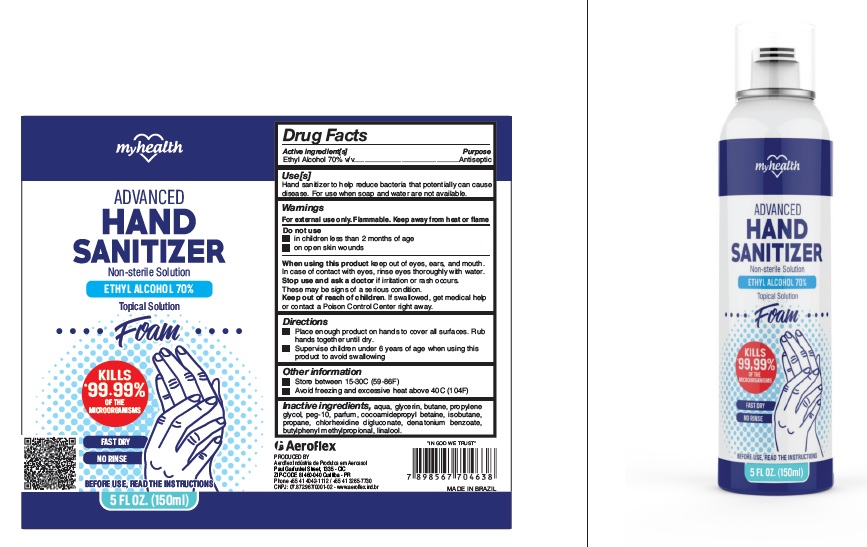 DRUG LABEL: MyHealth Advanced Hand Sanitizer
NDC: 80661-002 | Form: LIQUID
Manufacturer: Aeroflex Industria de Aerosol Ltda
Category: otc | Type: HUMAN OTC DRUG LABEL
Date: 20251031

ACTIVE INGREDIENTS: ALCOHOL 70 mL/100 mL
INACTIVE INGREDIENTS: WATER; GLYCERIN; BUTANE; PROPYLENE GLYCOL; POLYETHYLENE GLYCOL, UNSPECIFIED; SULFURYL FLUORIDE; COCAMIDOPROPYL BETAINE; ISOBUTANE; PROPANE; CHLORHEXIDINE GLUCONATE; DENATONIUM BENZOATE; BUTYLPHENYL METHYLPROPIONAL; LINALOOL, (+/-)-

MyHealth Advanced Hand Sanitizer

Active Ingredient

Ethyl Alcohol 70% v/v

Purpose

Antiseptic

Warnings

For external use only. Flammable. Keep away from heat or flame.

Do not use

- in children less than 2 months of age
- on open skin wounds

When using this productkeep out of eyes, ears, and mouth.

In case of contact with eyes, rinse eyes thoroughly with water.

Stop use and ask a doctorif irritation or rash occurs.These may be signs of a serious condition.

Keep out of reach of children.

If swallowed, get medical help or contact a Poison Control Center right away.

Uses

Hand sanitizer to help reduce bacteria that potentially can cause disease. For use when soap and water are not available.

Directions

- Place enough product on hands to cover all surfaces. Rub hands together until dry.
- Supervise children under 6 years of age when using this product to avoid swallowing.

Other Information

- Store between 15-30C (59-86F)
- Avoid freezing and excessive heat above 40C (104F)

Inactive Ingredients

aqua, glycerin, butane, propylene glycol, peg-10, parfum, cocoamidepropyl betaine,isobutane, propane, chlorhexidine digluconate, denatonium benzoate, butylphenyl,methylpropional, linalool.